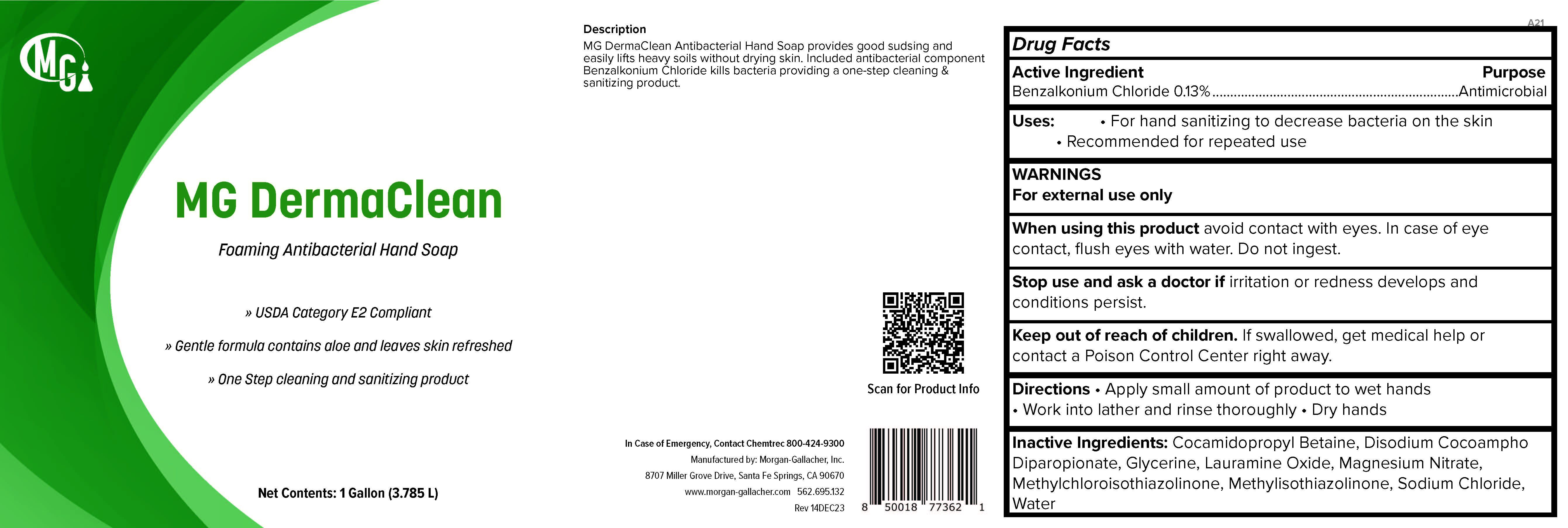 DRUG LABEL: MG DermaClean
NDC: 50241-014 | Form: LIQUID
Manufacturer: Morgan Gallacher Inc.
Category: otc | Type: HUMAN OTC DRUG LABEL
Date: 20251223

ACTIVE INGREDIENTS: BENZALKONIUM CHLORIDE 0.13 g/100 g
INACTIVE INGREDIENTS: COCAMIDOPROPYL BETAINE; DISODIUM COCOAMPHODIPROPIONATE; GLYCERIN; LAURAMINE OXIDE; MAGNESIUM NITRATE; METHYLCHLOROISOTHIAZOLINONE; METHYLISOTHIAZOLINONE; SODIUM CHLORIDE; WATER

MG DermaClean

Active Ingredient

Benzalkonium Chloride........0.13%

Uses

- For Hand sanitizing to decrease bacteria on the skin
- Recommended for repeated use

Purpsoe

Antimicrobial

Warnings

- For external use only
- When using this product avoid contact with eyes. In case of eye contact flush eyes with water. Do not ingest.
- Stop use and ask a doctor if irritation or redness develops and conditions persist.

Keep out of reach of children.

If swallowed, get medical help or contact a Poison Control Center right away.

Directions

- Apply small amount of product to wet hands
- Work into lather and rinse thoroughly
- Dry hands

Inactive Ingredients

- cocamidopropyl betaine
- disodium cocoamphodipropionate
- glycerin
- lauramine oxide
- magnesium nitrate
- methylchloroisothiazolinone
- methylisothiazolinone
- sodium chloride
- water